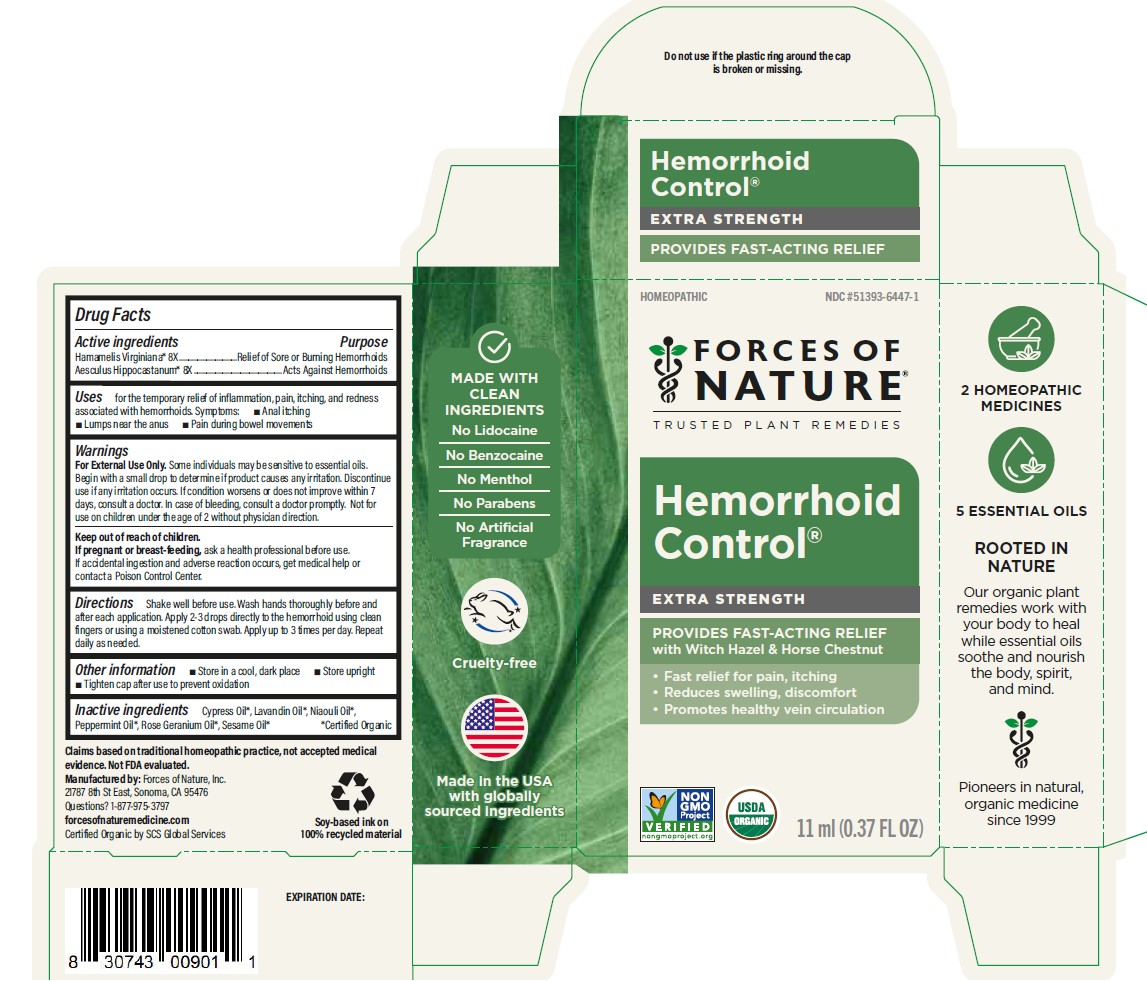 DRUG LABEL: Hemorrhoid Control
NDC: 51393-6447 | Form: SOLUTION/ DROPS
Manufacturer: Forces of Nature
Category: homeopathic | Type: HUMAN OTC DRUG LABEL
Date: 20260227

ACTIVE INGREDIENTS: HAMAMELIS VIRGINIANA ROOT BARK/STEM BARK 8 [hp_X]/1000 mL; HORSE CHESTNUT 8 [hp_X]/1000 mL
INACTIVE INGREDIENTS: GERANIUM OIL, ALGERIAN TYPE; LAVANDIN OIL; SESAME OIL; PEPPERMINT OIL; MELALEUCA QUINQUENERVIA LEAF OIL

Hemorrhoid Control
Extra Strength

Drug Facts

ACTIVE INGREDIENT

Active Ingredients | Purpose
Hamamelis Virginiana* 8X | Relief of Sore or Burning Hemorrhoids
Aesculus Hippocastanum* 8X | Acts Against Hemorrhoids

*Certified Organic

Inactive ingredients

Cypress Oil*, Lavandin Oil*, Niaouli Oil*, Peppermint Oil*, Rose Geranium Oil*, Sesame Oil*

*Certified Oil

Directions

Shake well before use. Wash hands thoroughly before and after each application. Apply 2 - 3 drops directly to the hemorrhoid using clean fingers or using a moistened cotton swab.Apply up to 3 times per day. Repeat daily as needed.

Uses

for the temporary relief of inflammation, pain, itching and redness associated with hemorrhoids.Symptoms:

- Anal itching
- Lumps near the anus
- Pain during bowel movements

Warnings

PREGNANCY OR BREAST FEEDING

If pregnant or breast-feeding, ask a health professional before use.

If accidental ingestion and adverse reaction occurs, get medical help or contact a Poison Control Center.

WHEN USING

For external use only. Some individuals may be sensitive to essential oils. Begin with a small drop to determine if product causes any irritation. Discontinue use if any irritation occurs. If condition worsens or does not improve, within 7 days, consult a doctor. Not for use on children under the age of 2 without physician direction.

Keep out of reach of children.

RECENT MAJOR CHANGES

Directions for use were made more complete for better user clarity and usage experience.

Indications were updated to Uses and expanded to specific symptoms for improved clarity.

PRINCIPAL DISPLAY PANEL - 11ml Bottle Label

HOMEOPATHIC

NDC 51393-6447-1

FORCES OF NATURE®

TRUSTED PLANT REMEDIES

Hemorrhoid Control®

EXTRA STRENGTH

PROVIDES FAST-ACTING RELIEF

with Witch Hazel & Horse Chestnut

- Fast relief for pain, itching
- Reduces swelling, discomfort
- Promotes healty vein circulation

NON

GMO

project

VERIFIED

nongmoproject.org

USDA
ORGANIC

11ml (0.37 FL OZ)